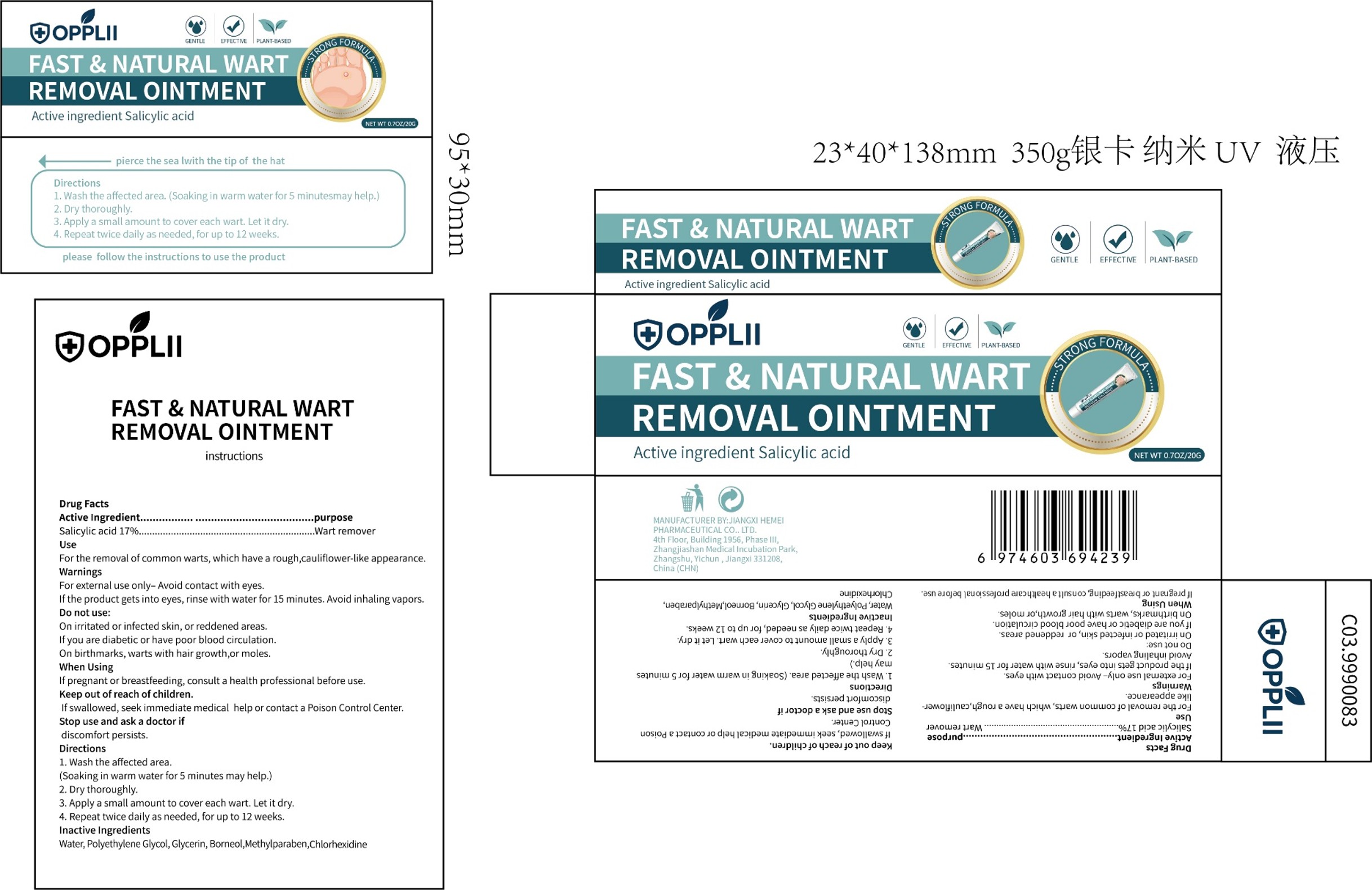 DRUG LABEL: FAST NATURAL WART REMOVAL
NDC: 85825-001 | Form: OINTMENT
Manufacturer: Shenzhen Haizhida E-commerce Co., Ltd
Category: otc | Type: HUMAN OTC DRUG LABEL
Date: 20250625

ACTIVE INGREDIENTS: SALICYLIC ACID 17 g/100 g
INACTIVE INGREDIENTS: WATER; POLYETHYLENE GLYCOL, UNSPECIFIED; BORNEOL; CHLORHEXIDINE; GLYCERIN; METHYLPARABEN

85825-001 FAST NATURAL WART REMOVAL

ACTIVE INGREDIENT

Salicylic Acid 17%

PURPOSE

Wart remover

INDICATIONS AND USAGE

For the removal of common warts, which have a rough,cauliflower-like appearance.

WARNINGS

For external use only- Avoid contact with eyes.
lf the product gets into eyes, rinse with water for 15 minutes. Avoid inhaling vapors.

DO NOT USE

On irritated or infected skin, or reddened areas.
lf you are diabetic or have poor blood circulation.
On birthmarks, warts with hair growth,or moles.

WHEN USING

lf pregnant or breastfeeding, consult a health professional before use.

STOP USE

discomfort persists.

KEEP OUT OF REACH OF CHILDREN

lf swallowed, seek immediate medical help or contact a Poison Control Center.

DOSAGE AND ADMINISTRATION

1. Wash the affected area.
(Soaking in warm water for 5 minutes may help.)
2. Dry thoroughly.
3. Apply a small amount to cover each wart. Let it dry.
4. Repeat twice daily as needed, for up to 12 weeks.

INACTIVE INGREDIENT

Water
Polyethylene Glycol
Glycerin
Borneol
Methylparaben
Chlorhexidine